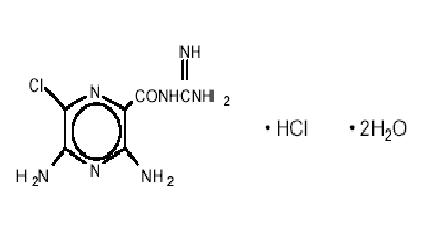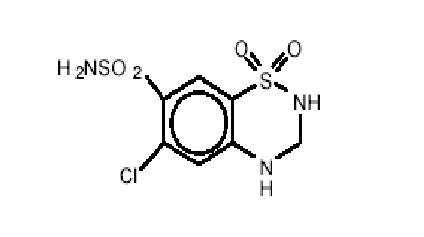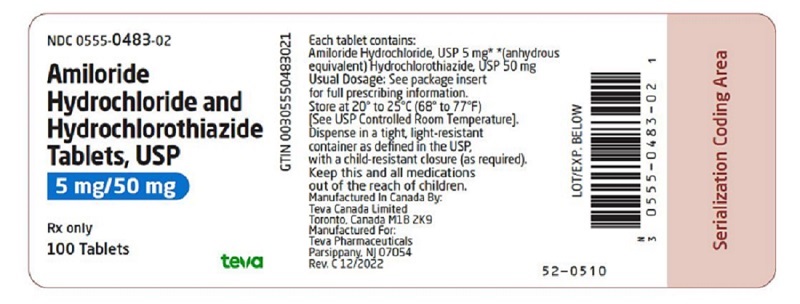 DRUG LABEL: Amiloride Hydrochloride and Hydrochlorothiazide
NDC: 0555-0483 | Form: TABLET
Manufacturer: Teva Pharmaceuticals USA, Inc.
Category: prescription | Type: HUMAN PRESCRIPTION DRUG LABEL
Date: 20221227

ACTIVE INGREDIENTS: AMILORIDE HYDROCHLORIDE 5 mg/1 1; HYDROCHLOROTHIAZIDE 50 mg/1 1
INACTIVE INGREDIENTS: CROSCARMELLOSE SODIUM; D&C YELLOW NO. 10 ALUMINUM LAKE; ALUMINUM OXIDE; LACTOSE MONOHYDRATE; MAGNESIUM OXIDE; MAGNESIUM STEARATE; CELLULOSE, MICROCRYSTALLINE

Amiloride Hydrochloride and Hydrochlorothiazide Tablets, USP

5 mg/50 mg

Rx only

DESCRIPTION

Amiloride hydrochloride and hydrochlorothiazide tablets, USP combine the potassium-conserving action of amiloride hydrochloride with the natriuretic action of hydrochlorothiazide.

Amiloride HCl, USP is designated chemically as N-amidino-3,5,-diamino-6-chloropyrazine-carboxamide monohydrochloride dihydrate and its structural formula is:

C6H8CIN7O•HCl•2H2O M.W. 302.12

Hydrochlorothiazide, USP is designated chemically as 6-chloro-3,4-dihydro-2H-1, 2, 4-benzo-thiadiazine-7-sulfonamide 1, 1-dioxide. Its structural formula is:

C7H8CIN3O4S2 M.W. 297.74

It is a white, or practically white, crystalline powder which is slightly soluble in water, but freely soluble in sodium hydroxide solution.

Each tablet, for oral administration, contains 5 mg of amiloride hydrochloride, USP (calculated on the anhydrous basis) and 50 mg of hydrochlorothiazide, USP.

Inactive Ingredients: Croscarmellose sodium, D&C yellow no. 10 (aluminum lake), lactose monohydrate, magnesium oxide, magnesium stearate, microcrystalline cellulose.

CLINICAL PHARMACOLOGY

Amiloride hydrochloride and hydrochlorothiazide tablets provide diuretic and antihypertensive activity (principally due to the hydrochlorothiazide component), while acting through the amiloride component to prevent the excessive potassium loss that may occur in patients receiving a thiazide diuretic. Due to its amiloride component, the urinary excretion of magnesium is less with amiloride and hydrochlorothiazide than with a thiazide or loop diuretic used alone (see PRECAUTIONS). The onset of the diuretic action of this product is within 1 to 2 hours and this action appears to be sustained for approximately 24 hours.

Amiloride Hydrochloride

Amiloride Hydrochloride is a potassium-conserving (antikaliuretic) drug that possesses weak (compared with thiazide diuretics) natriuretic, diuretic, and antihypertensive activity. These effects have been partially additive to the effects of thiazide diuretics in some clinical studies. Amiloride HCl has potassium-conserving activity in patients receiving kaliuretic-diuretic agents.

Amiloride HCl is not an aldosterone antagonist and its effects are seen even in the absence of aldosterone.

Amiloride HCl exerts its potassium-sparing effect through the inhibition of sodium reabsorption at the distal convoluted tubule, cortical collecting tubule and collecting duct; this decreases the net negative potential of the tubular lumen and reduces both potassium and hydrogen secretion and their subsequent excretion. This mechanism accounts in large part for the potassium-sparing action of amiloride.

Amiloride HCl usually begins to act within two hours after an oral dose. Its effect on electrolyte excretion reaches a peak between 6 to 10 hours and lasts about 24 hours. Peak plasma levels are obtained in 3 to 4 hours and the plasma half-life varies from 6 to 9 hours. Effects on electrolytes increase with single doses of amiloride hydrochloride up to approximately 15 mg.

Amiloride HCl is not metabolized by the liver but is excreted unchanged by the kidneys. About 50 percent of a 20 mg dose of amiloride hydrochloride is excreted in the urine and 40 percent in the stool within 72 hours. Amiloride HCl has little effect on glomerular filtration rate or renal blood flow. Because amiloride HCl is not metabolized by the liver, drug accumulation is not anticipated in patients with hepatic dysfunction, but accumulation can occur if the hepatorenal syndrome develops.

Hydrochlorothiazide

The mechanism of the antihypertensive effect of thiazides is unknown. Thiazides do not usually affect normal blood pressure.

Hydrochlorothiazide is a diuretic and antihypertensive. It affects the distal renal tubular mechanism of electrolyte reabsorption. Hydrochlorothiazide increases excretion of sodium and chloride in approximately equivalent amounts. Natriuresis may be accompanied by some loss of potassium and bicarbonate.

After oral administration diuresis begins within two hours, peaks in about four hours and lasts about 6 to 12 hours.

Hydrochlorothiazide is not metabolized but is eliminated rapidly by the kidney. When plasma levels have been followed for at least 24 hours, the plasma half-life has been observed to vary between 5.6 and 14.8 hours. At least 61 percent of the oral dose is eliminated unchanged within 24 hours. Hydrochlorothiazide crosses the placental but not the blood-brain barrier and is excreted in breast milk.

INDICATIONS AND USAGE

Amiloride hydrochloride and hydrochlorothiazide tablets are indicated in those patients with hypertension or with congestive heart failure who develop hypokalemia when thiazides or other kaliuretic diuretics are used alone, or in whom maintenance of normal serum potassium levels is considered to be clinically important, e.g., digitalized patients, or patients with significant cardiac arrhythmias.

The use of potassium-conserving agents is often unnecessary in patients receiving diuretics for uncomplicated essential hypertension when such patients have a normal diet.

Amiloride hydrochloride and hydrochlorothiazide tablets may be used alone or as an adjunct to other antihypertensive drugs, such as methyldopa or beta blockers. Since amiloride hydrochloride and hydrochlorothiazide enhances the action of these agents, dosage adjustments may be necessary to avoid an excessive fall in blood pressure and other unwanted side effects.

The fixed combination drug is not indicated for the initial therapy of edema or hypertension except in individuals in whom the development of hypokalemia cannot be risked.

CONTRAINDICATIONS

Hyperkalemia

Amiloride hydrochloride and hydrochlorothiazide tablets should not be used in the presence of elevated serum potassium levels (greater than 5.5 mEq per liter).

Antikaliuretic Therapy or Potassium Supplementation

Amiloride hydrochloride and hydrochlorothiazide should not be given to patients receiving other potassium-conserving agents, such as spironolactone or triamterene. Potassium supplementation in the form of medication, potassium-containing salt substitutes or a potassium-rich diet should not be used with this product except in severe and/or refractory cases of hypokalemia. Such concomitant therapy can be associated with rapid increases in serum potassium levels. If potassium supplementation is used, careful monitoring of the serum potassium level is necessary.

Impaired Renal Function

Anuria, acute or chronic renal insufficiency, and evidence of diabetic nephropathy are contraindications to the use of amiloride hydrochloride and hydrochlorothiazide. Patients with evidence of renal function impairment (blood urea nitrogen [BUN] levels over 30 mg per 100 mL or serum creatinine levels over 1.5 mg per 100 mL) or diabetes mellitus should not receive the drug without careful, frequent and continuing monitoring of serum electrolytes, creatinine, and BUN levels. Potassium retention associated with the use of an antikaliuretic agent is accentuated in the presence of renal impairment and may result in the rapid development of hyperkalemia.

Hypersensitivity

Amiloride hydrochloride and hydrochlorothiazide tablets is contraindicated in patients who are hypersensitive to this product, or to other sulfonamide-derived drugs.

WARNINGS

Hyperkalemia

BOXED WARNING

Like other potassium-conserving diuretic combinations, amiloride and hydrochlorothiazide may cause hyperkalemia (serum potassium levels greater than 5.5 mEq per liter). In patients without renal impairment or diabetes mellitus, the risk of hyperkalemia with this combination product is about 1 to 2 percent. This risk is higher in patients with renal impairment or diabetes mellitus (even without recognized diabetic nephropathy). Since hyperkalemia, if uncorrected, is potentially fatal, it is essential to monitor serum potassium levels carefully in any patient receiving amiloride hydrochloride and hydrochlorothiazide, particularly when it is first introduced, at the time of dosage adjustments, and during any illness that could affect renal function.

The risk of hyperkalemia may be increased when potassium-conserving agents, including amiloride hydrochloride and hydrochlorothiazide, are administered concomitantly with an angiotensin-converting enzyme inhibitor, cylosporine or tacrolimus (see PRECAUTIONS, Drug Interactions). Warning signs or symptoms of hyperkalemia include paresthesias, muscular weakness, fatigue, flaccid paralysis of the extremities, bradycardia, shock, and ECG abnormalities. Monitoring of the serum potassium level is essential because mild hyperkalemia is not usually associated with an abnormal ECG.

When abnormal, the ECG in hyperkalemia is characterized primarily by tall, peaked T waves or elevations from previous tracings. There may also be lowering of the R wave and increased depth of the S wave, widening and even disappearance of the P wave, progressive widening of the QRS complex, prolongation of the PR interval, and ST depression.

Treatment of Hyperkalemia

If hyperkalemia occurs in patients taking amiloride and hydrochlorothiazide, the drug should be discontinued immediately. If the serum potassium level exceeds 6.5 mEq per liter, active measures should be taken to reduce it. Such measures include the intravenous administration of sodium bicarbonate solution or oral or parenteral glucose with a rapid-acting insulin preparation. If needed, a cation exchange resin such as sodium polystyrene sulfonate may be given orally or by enema. Patients with persistent hyperkalemia may require dialysis.

Diabetes Mellitus

In diabetic patients, hyperkalemia has been reported with the use of all potassium-conserving diuretics, including amiloride HCl, even in patients without evidence of diabetic nephropathy. Therefore, amiloride and hydrochlorothiazide should be avoided, if possible, in diabetic patients and, if it is used, serum electrolytes and renal function must be monitored frequently.

Amiloride and hydrochlorothiazide should be discontinued at least three days before glucose tolerance testing.

Metabolic or Respiratory Acidosis

Antikaliuretic therapy should be instituted only with caution in severely ill patients in whom respiratory or metabolic acidosis may occur, such as patients with cardiopulmonary disease or poorly controlled diabetes. If amiloride and hydrochlorothiazide is given to these patients, frequent monitoring of acid-base balance is necessary. Shifts in acid-base balance alter the ratio of extracellular/intracellular potassium, and the development of acidosis may be associated with rapid increases in serum potassium levels.

PRECAUTIONS

General

Electrolyte Imbalance and BUN Increases

Determination of serum electrolytes to detect possible electrolyte imbalance should be performed at appropriate intervals.

Patients should be observed for clinical signs of fluid or electrolytes imbalance: i.e., hyponatremia, hypochloremic alkalosis, and hypokalemia. Serum and urine electrolyte determinations are particularly important when the patient is vomiting excessively or receiving parenteral fluids. Warning signs or symptoms of fluid and electrolyte imbalance, irrespective of cause, include dryness of mouth, thirst, weakness, lethargy, drowsiness, restlessness, confusion, seizures, muscle pains or cramps, muscular fatigue, hypotension, oliguria, tachycardia, and gastrointestinal disturbances such as nausea and vomiting.

Hyponatremia and hypochloremia may occur during the use of thiazides and other diuretics. Any chloride deficit during thiazide therapy is generally mild and may be lessened by the amiloride HCl component of this product. Hypochloremia usually does not require specific treatment except under extraordinary circumstances (as in liver disease or renal disease). Dilutional hyponatremia may occur in edematous patients in hot weather; appropriate therapy is water restriction, rather than administration of salt, except in rare instances when the hyponatremia is life threatening. In actual salt depletion, appropriate replacement is the therapy of choice.

Hypokalemia may develop during thiazide therapy, especially with brisk diuresis, when severe cirrhosis is present, during concomitant use of corticosteroids or ACTH, or after prolonged therapy. However, this usually is prevented by the amiloride hydrochloride component of this combination drug product.

Interference with adequate oral electrolyte intake will also contribute to hypokalemia. Hypokalemia may cause cardiac arrhythmia and may also sensitize or exaggerate the response of the heart to the toxic effects of digitalis (e.g., increased ventricular irritability).

Thiazides have been shown to increase the urinary excretion of magnesium; this may result in hypomagnesemia. Amiloride hydrochloride, a component of this combination product, has been shown to decrease the enhanced urinary excretion of magnesium which occurs when a thiazide or loop diuretic is used alone.

Increases in BUN levels have been reported with amiloride hydrochloride and with hydrochlorothiazide. These increases usually have accompanied vigorous fluid elimination, especially when diuretic therapy was used in seriously ill patients, such as those who had hepatic cirrhosis with ascites and metabolic alkalosis, or those with resistant edema. Therefore, when amiloride and hydrochlorothiazide is given to such patients, careful monitoring of serum electrolyte and BUN levels is important. In patients with pre-existing severe liver disease, hepatic encephalopathy, manifested by tremors, confusion, and coma, and increased jaundice, have been reported in association with diuretic therapy including amiloride HCl and hydrochlorothiazide.

In patients with renal disease, diuretics may precipitate azotemia. Cumulative effects of the components of amiloride hydrochloride and hydrochlorothiazide may develop in patients with impaired renal function. If renal impairment becomes evident, amiloride and hydrochlorothiazide should be discontinued (see CONTRAINDICATIONS and WARNINGS).

Information for Patients

Non-melanoma Skin Cancer: Instruct patients taking hydrochlorothiazide to protect skin from the sun and undergo regular skin cancer screening.

Drug Interactions

In some patients, the administration of a non-steroidal anti-inflammatory agent can reduce the diuretic, natriuretic, and antihypertensive effects of loop, potassium-sparing and thiazide diuretics. Therefore, when amiloride and hydrochlorothiazide plus non-steroidal anti-inflammatory agents are used concomitantly, the patient should be observed closely to determine if the desired effect of the diuretic is obtained. Since indomethacin and potassium-sparing diuretics, including this product, may each be associated with increased serum potassium levels, the potential effects on potassium kinetics and renal function should be considered when these agents are administered concurrently.

Amiloride HCl

When amiloride HCl is administered concomitantly with an angiotensin-converting enzyme inhibitor, cyclosporine or tacrolimus, the risk of hyperkalemia may be increased. Therefore, if concomitant use of these agents is indicated because of demonstrated hypokalemia, they should be used with caution and with frequent monitoring of serum potassium (see WARNINGS).

Hydrochlorothiazide

When given concurrently the following drugs may interact with thiazide diuretics.

Alcohol, Barbiturates, or Narcotics

Potentiation of orthostatic hypotension may occur.

Antidiabetic Drugs (Oral Agents and Insulin)

Dosage adjustment of the antidiabetic drug may be required.

Other Antihypertensive Drugs

Additive effect or potentiation.

Cholestyramine and Colestipol Resins

Absorption of hydrochlorothiazide is impaired in the presence of anionic exchange resins. Single doses of cholestyramine and colestipol resins bind the hydrochlorothiazide and reduce its absorption from the gastrointestinal tract by up to 85 and 43 percent, respectively.

Corticosteroids, ACTH

Intensified electrolyte depletion, particularly hypokalemia.

Pressor Amines (e.g., norepinephrine)

Possible decreased response to pressor amines but not sufficient to preclude their use.

Skeletal Muscle Relaxants, Nondepolarizing (e.g., tubocurarine)

Possible increased responsiveness to the muscle relaxant.

Lithium

Generally should not be given with diuretics. Diuretic agents reduce the renal clearance of lithium and add a high risk of lithium toxicity. Refer to the package insert for lithium preparations before use of such preparations with this combination product.

Metabolic and Endocrine Effects

In diabetic patients, insulin requirements may be increased, decreased, or unchanged due to the hydrochlorothiazide component. Diabetes mellitus that has been latent may become manifest during administration of thiazide diuretics.

Because calcium excretion is decreased by thiazides, amiloride and hydrochlorothiazide should be discontinued before carrying out tests for parathyroid function. Pathologic changes in the parathyroid glands, with hypercalcemia and hypophosphatemia have been observed in a few patients on prolonged thiazide therapy; however, the common complications of hyperparathyroidism such as renal lithiasis, bone resorption, and peptic ulceration have not been seen.

Hyperuricemia may occur or acute gout may be precipitated in certain patients receiving thiazide therapy.

Other Precautions

In patients receiving thiazides, sensitivity reactions may occur with or without a history of allergy or bronchial asthma. The possibility of exacerbation or activation of systemic lupus erythematosus has been reported with the use of thiazides.

Increases in cholesterol and triglyceride levels may be associated with thiazide diuretic therapy.

Carcinogenesis, Mutagenicity, Impairment of Fertility

Long-term studies in animals have not been performed to evaluate the effects upon fertility, mutagenicity or carcinogenic potential of amiloride hydrochloride and hydrochlorothiazide.

Amiloride HCl

There was no evidence of a tumorigenic effect when amiloride hydrochloride was administered for 92 weeks to mice at doses up to 10 mg/kg/day (25 times the maximum daily human dose). Amiloride hydrochloride has also been administered for 104 weeks to male and female rats at doses up to 6 and 8 mg/kg/day (15 and 20 times the maximum daily dose for humans, respectively) and showed no evidence of carcinogenicity.

Amiloride hydrochloride was devoid of mutagenic activity in various strains of Salmonella typhimurium with or without a mammalian liver microsomal activation system (Ames test).

Hydrochlorothiazide

Two-year feeding studies in mice and rats conducted under the auspices of the National Toxicology Program (NTP) uncovered no evidence of a carcinogenic potential of hydrochlorothiazide in female mice (at doses of up to approximately 600 mg/kg/day) or in male and female rats (at doses up to approximately 100 mg/kg/day). The NTP, however, found equivocal evidence for hepatocarcinogenicity in male mice.

Hydrochlorothiazide was not genotoxic in vitro in the Ames mutagenicity assay of Salmonella typhimurium strains TA 98, TA 100, TA 1535, TA 1537, and TA 1538 and in the Chinese Hamster Ovary (CHO) test for chromosomal aberrations, or in vivo in assays using mouse germinal cell chromosomes, Chinese Hamster bone marrow chromosomes, and the Drosophila sex-linked recessive lethal trait gene. Positive test results were obtained only in the in vitro CHO Sister Chromatid Exchange (clastogenicity) and in the Mouse Lymphoma Cell (mutagenicity) assays, using concentrations of hydrochlorothiazide from 43 to 1300 mcg/mL, and in the Aspergillus nidulans non-disjunction assay at an unspecified concentration.

Hydrochlorothiazide had no adverse effects on the fertility of mice and rats of either sex in studies wherein these species were exposed, via their diet, to doses of up to 100 and 4 mg/kg, respectively, prior to conception and throughout gestation.

Teratogenic Effects

Teratogenicity studies have been performed with combinations of amiloride hydrochloride and hydrochlorothiazide in rabbits and mice at doses up to 25 times the expected maximum daily dose for humans and have revealed no evidence of harm to the fetus. No evidence of impaired fertility in rats was apparent at dosage levels up to 25 times the expected maximum human daily dose. A perinatal and postnatal study in rats showed a reduction in maternal body weight gain during and after gestation at a daily dose of 25 times the expected maximum daily dose for humans. The body weights of alive pups at birth and at weaning were also reduced at this dose level. There are no adequate and well-controlled studies in pregnant women. Because animal reproduction studies are not always predictive of human responses, and because of the data listed below with the individual components, this drug should be used during pregnancy only if clearly needed.

Amiloride Hydrochloride

Teratogenicity studies with amiloride hydrochloride in rabbits and mice given 20 and 25 times the maximum human dose, respectively, revealed no evidence of harm to the fetus, although studies showed that the drug crossed the placenta in modest amounts. Reproduction studies in rats at 20 times the expected maximum daily dose for humans showed no evidence of impaired fertility. At approximately 5 or more times the expected maximum daily dose for humans, some toxicity was seen in adult rats and rabbits and a decrease in rat pup growth and survival occurred.

Teratogenic Effects

Studies in which hydrochlorothiazide was orally administered to pregnant mice and rats during their respective periods of major organogenesis at doses up to 3000 and 1000 mg hydrochlorothiazide/kg, respectively, provided no evidence of harm to the fetus. There are, however, no adequate and well-controlled studies in pregnant women.

Nonteratogenic Effects

Thiazides cross the placental barrier and appear in cord blood. There is a risk of fetal or neonatal jaundice, thrombocytopenia, and possibly other adverse reactions that have occurred in adults.

Nursing Mothers

Studies in rats have shown that amiloride is excreted in milk in concentrations higher than those found in blood, but it is not known whether amiloride HCl is excreted in human milk. However, thiazides appear in breast milk. Because of the potential for serious adverse reactions in nursing infants, a decision should be made whether to discontinue nursing or to discontinue the drug, taking into account the importance of the drug to the mother.

Pediatric Use

Safety and effectiveness in pediatric patients have not been established.

Geriatric Use

Clinical studies of amiloride hydrochloride and hydrochlorothiazide tablets did not include sufficient numbers of subjects aged 65 and over to determine whether they responded differently from younger subjects. Other reported clinical experience has not identified differences in responses between the elderly and younger patients. In general, dose selection for an elderly patient should be cautious, usually starting at the low end of the dosing range, reflecting the greater frequency of decreased hepatic, renal or cardiac function, and the comitant disease or other drug therapy.

This drug is known to be substantially excreted by the kidney, and the risk of toxic reactions to this drug may be greater in patients with impaired renal function. Because elderly patients are more likely to have decreased renal function, care should be taken in dose selection, and it may be useful to monitor renal function (see CONTRAINDICATIONS, Impaired Renal Function).

ADVERSE REACTIONS

Amiloride hydrochloride and hydrochlorothiazide is usually well tolerated and significant clinical adverse effects have been reported infrequently. The risk of hyperkalemia (serum potassium levels greater than 5.5 mEq per liter) with amiloride hydrochloride and hydrochlorothiazide is about 1 to 2 percent in patients without renal impairment or diabetes mellitus (see WARNINGS). Minor adverse reactions to amiloride hydrochloride have been reported relatively frequently (about 20%) but the relationship of many of the reports to amiloride HCl is uncertain and the overall frequency was similar to hydrochlorothiazide treated groups. Nausea/anorexia, abdominal pain, flatulence, and mild skin rash have been reported and probably are related to amiloride. Other adverse experiences that have been reported with amiloride and hydrochlorothiazide are generally those known to be associated with diuresis, thiazide therapy, or with the underlying disease being treated. Clinical trials have not demonstrated that combining amiloride and hydrochlorothiazide increases the risk of adverse reactions over those seen with the individual components.

The adverse reactions for amiloride and hydrochlorothiazide listed in the following table have been arranged into two groups: (1) incidence greater than one percent; and (2) incidence one percent or less. The incidence for group (1) was determined from clinical studies conducted in the United States (607 patients treated with amiloride and hydrochlorothiazide). The adverse effects listed in group (2) include reports from the same clinical studies and voluntary reports since marketing. The probability of a causal relationship exists between amiloride and hydrochlorothiazide and these adverse reactions, some of which have been reported only rarely.

Incidence > 1% | Incidence ≤ 1%
Body as a Whole
Headache^1 Weakness^1; Fatigue/tiredness | Malaise Chest pain Back pain Syncope
Cardiovascular
Arrhythmia | Tachycardia Digitalis toxicity Orthostatic hypotension Angina pectoris
Digestive
Nausea/anorexia^1 Diarrhea Gastrointestinal pain Abdominal pain | Constipation GI bleeding GI disturbance Appetite changes Abdominal fullness Hiccups Thirst Vomiting Anorexia Flatulence
Metabolic
Elevated serum potassium levels (> 5.5 mEq per liter)^2 | Gout Dehydration Symptomatic hyponatremia^3
Musculoskeletal
Leg ache | Muscle cramps/spasm Joint pain
Nervous
Dizziness^1 | Paresthesia/numbness Stupor Vertigo
Psychiatric None | Insomnia Nervousness Depression Sleepiness Mental confusion
Respiratory
Dyspnea | None
Skin
Rash^1 Pruritus | Flushing Diaphoresis Erythema multiforme including Stevens- Johnson syndrome Exfoliative dermatitis including toxic epidermal necrolysis Alopecia
Special Senses
None | Bad taste Visual disturbance Nasal congestion
Urogenital
None | Impotence Nocturia Dysuria Incontinence Renal dysfunction including renal failure Gynecomastia

^1. Reactions occurring in 3% to 8% of patients treated with amiloride hydrochloride and hydrochlorothiazide. (Those reactions occurring in less than 3% of the patients are unmarked.)

^2. See WARNINGS

^3. See PRECAUTIONS

Other adverse reactions that have been reported with the individual components and within each category are listed in order of decreasing severity:

Amiloride

Body as a Whole: Painful extremities, neck/shoulder ache, fatigability.

Cardiovascular: Palpitation.

Digestive: Activation of probable pre-existing peptic ulcer, abnormal liver function, jaundice, dyspepsia, heartburn.

Hematologic: Aplastic anemia, neutropenia.

Integumentary: Alopecia, itching, dry mouth.

Nervous System/Psychiatric: Encephalopathy, tremors, decreased libido.

Respiratory: Shortness of breath, cough.

Special Senses: Increased intraocular pressure, tinnitus.

Urogenital: Bladder spasms, polyuria, urinary frequency.

Hydrochlorothiazide

Digestive: Pancreatitis, jaundice (intrahepatic cholestatic jaundice), sialadenitis, cramping, gastric irritation.

Hematologic: Aplastic anemia, agranulocytosis, leukopenia, hemolytic anemia, thrombocytopenia.

Hypersensitivity: Anaphylactic reactions, necrotizing angiitis (vasculitis, cutaneous vasculitis), respiratory distress including pneumonitis and pulmonary edema, photosensitivity, fever, urticaria, purpura.

Metabolic: Electrolyte imbalance (see PRECAUTIONS), hyperglycemia, glycosuria, hyperuricemia.

Nervous System/Psychiatric: Restlessness.

Special Senses: Transient blurred vision, xanthopsia.

Urogenital: Interstitial nephritis (see WARNINGS).

Postmarketing Experience

Non-melanoma Skin Cancer

Hydrochlorothiazide is associated with an increased risk of non-melanoma skin cancer. In a study conducted in the Sentinel System, increased risk was predominantly for squamous cell carcinoma (SCC) and in white patients taking large cumulative doses. The increased risk for SCC in the overall population was approximately 1 additional case per 16,000 patients per year, and for white patients taking a cumulative dose of ≥ 50,000 mg the risk increase was approximately 1 additional SCC case for every 6,700 patients per year.

To report SUSPECTED ADVERSE REACTIONS, contact Teva at 1-888-838-2872 or FDA at 1-800-FDA-1088 or http://www.fda.gov/medwatch.

OVERDOSAGE

No data are available in regard to overdosage in humans. The oral LD50 of the combination drug is 189 and 422 mg/kg for female mice and female rats, respectively.

It is not known whether the drug is dialyzable.

No specific information is available on the treatment of overdosage with amiloride and hydrochlorothiazide and no specific antidote is available. Treatment is symptomatic and supportive. Therapy with amiloride and hydrochlorothiazide should be discontinued and the patient observed closely. Suggested measures include the induction of emesis and/or gastric lavage.

Amiloride Hydrochloride

No data are available in regard to overdosage in humans.

The oral LD50 of amiloride hydrochloride (calculated as the base) is 56 mg/kg in mice and 36 to 85 mg/kg in rats, depending on the strain.

The most common signs and symptoms to be expected with overdosage are dehydration and electrolyte imbalance. If hyperkalemia occurs, active measures should be taken to reduce the serum potassium levels.

Hydrochlorothiazide

The oral LD50 of hydrochlorothiazide is greater than 10 g/kg in both mice and rats.

The most common signs and symptoms observed are those caused by electrolyte depletion (hypokalemia, hypochloremia, hyponatremia) and dehydration resulting from excessive diuresis. If digitalis has also been administered, hypokalemia may accentuate cardiac arrhythmias.

DOSAGE AND ADMINISTRATION

Amiloride hydrochloride and hydrochlorothiazide tablets should be administered with food.

The usual starting dosage is 1 tablet a day. The dosage may be increased to 2 tablets a day, if necessary. More than 2 tablets of amiloride hydrochloride and hydrochlorothiazide daily usually are not needed and there is no controlled experience with such doses.

Hydrochlorothiazide can be given at doses of 12.5 to 50 mg per day when used alone. Patients usually do not require doses of hydrochlorothiazide in excess of 50 mg daily when combined with other antihypertensive agents. The daily dose is usually given as a single dose but may be given in divided doses. Once an initial diuresis has been achieved, dosage adjustment may be necessary. Maintenance therapy may be on an intermittent basis.

HOW SUPPLIED

Amiloride hydrochloride and hydrochlorothiazide tablets, USP are available as:

5 mg/50 mg: | Light yellow, round, scored, biconvex tablet. Debossed with 555 over 483 on the scored side and stylized barr on the other side. Each tablet contains 5 mg of anhydrous amiloride HCl, USP and 50 mg of hydrochlorothiazide, USP.
 | 100 Tablets NDC 0555-0483-02; 1000 Tablets NDC 0555-0483-05

Dispense in a tight, light-resistant container as defined in the USP, with a child-resistant closure (as required).

Store at 20º to 25ºC (68º to 77ºF) [See USP Controlled Room Temperature].

Keep this and all medications out of the reach of children.

Manufactured In Canada By:

Teva Canada Limited

Toronto, Canada M1B 2K9

Manufactured For:

Teva Pharmaceuticals

Parsippany, NJ 07054

Rev. D 12/2022

Package/Label Display Panel

NDC 0555-0483-02
Amiloride Hydrochloride and Hydrochlorothiazide Tablets, USP
5 mg/50 mg
Rx only
100 Tablets